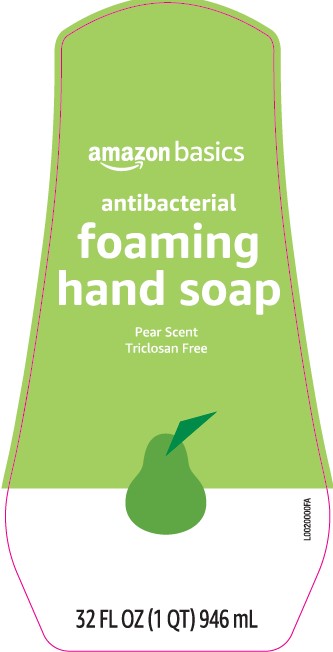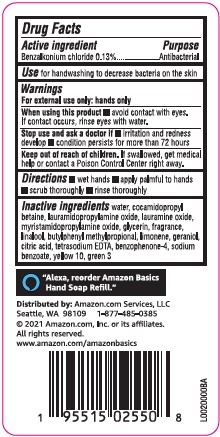 DRUG LABEL: Hand Wash
NDC: 72288-575 | Form: LIQUID
Manufacturer: Amozon.com Services LLC
Category: otc | Type: HUMAN OTC DRUG LABEL
Date: 20250424

ACTIVE INGREDIENTS: BENZALKONIUM CHLORIDE 1.3 mg/1 mL
INACTIVE INGREDIENTS: WATER; COCAMIDOPROPYL BETAINE; LAURAMIDOPROPYLAMINE OXIDE; LAURAMINE OXIDE; MYRISTAMIDOPROPYLAMINE OXIDE; GLYCERIN; LINALOOL, (+/-)-; BUTYLPHENYL METHYLPROPIONAL; LIMONENE, (+)-; GERANIOL; CITRIC ACID MONOHYDRATE; EDETATE SODIUM; SULISOBENZONE; SODIUM BENZOATE; FD&C GREEN NO. 3; D&C YELLOW NO. 10

Basics 575.002/575AD
Pear Foaming Antibacterial Hand Wash

Active ingredient

Benzalkonium chloride 0.13%

Purpose

Antibacterial

Use

for handwashing to decrease bacteria on the skin

warnings

For external use only: hands only

When using this product

- avoid contact with eyes. If contact occurs, rinse eyes thoroughly with water.

Stop use and ask a doctor if

- irritation and redness develop
- condition persists for more than 72 hours

Keep out of reach of children.

If swallowed, get medical help or contact a Poison Control Center right away.

Directions

- wet hands
- apply palmful to hands
- scrub thoroughly
- rinse thoroughly

Inactive ingredients

water, cocamidopropyl betaine, lauramidopropylamine oxide, lauramine oxide, myristamidopropylamine oxide, glycerin, fragrance, linalool, butylphenyl methylpropional, limonene, geraniol, citric acid, tetrasodium EDTA, benzophenone-4, sodium benzoate, yellow 10, green 3

Adverse Reactions

"Alexa, reorder Amazon Basics Hand Soap Refill."

DISTRIBUTED BY: Amazon.com Services, LLC

Seattle, WA 98109 1-877-485-0385

2021 Amazon.com, Inc. or its affiliates.

All rights reserved.

www.amazon.com/amazonbasics

principal display panel

amazon basics

antibacterial

foaming

hand soap

Pear Scent

Triclosan Free

32 FL OZ (1 QT) 946 mL